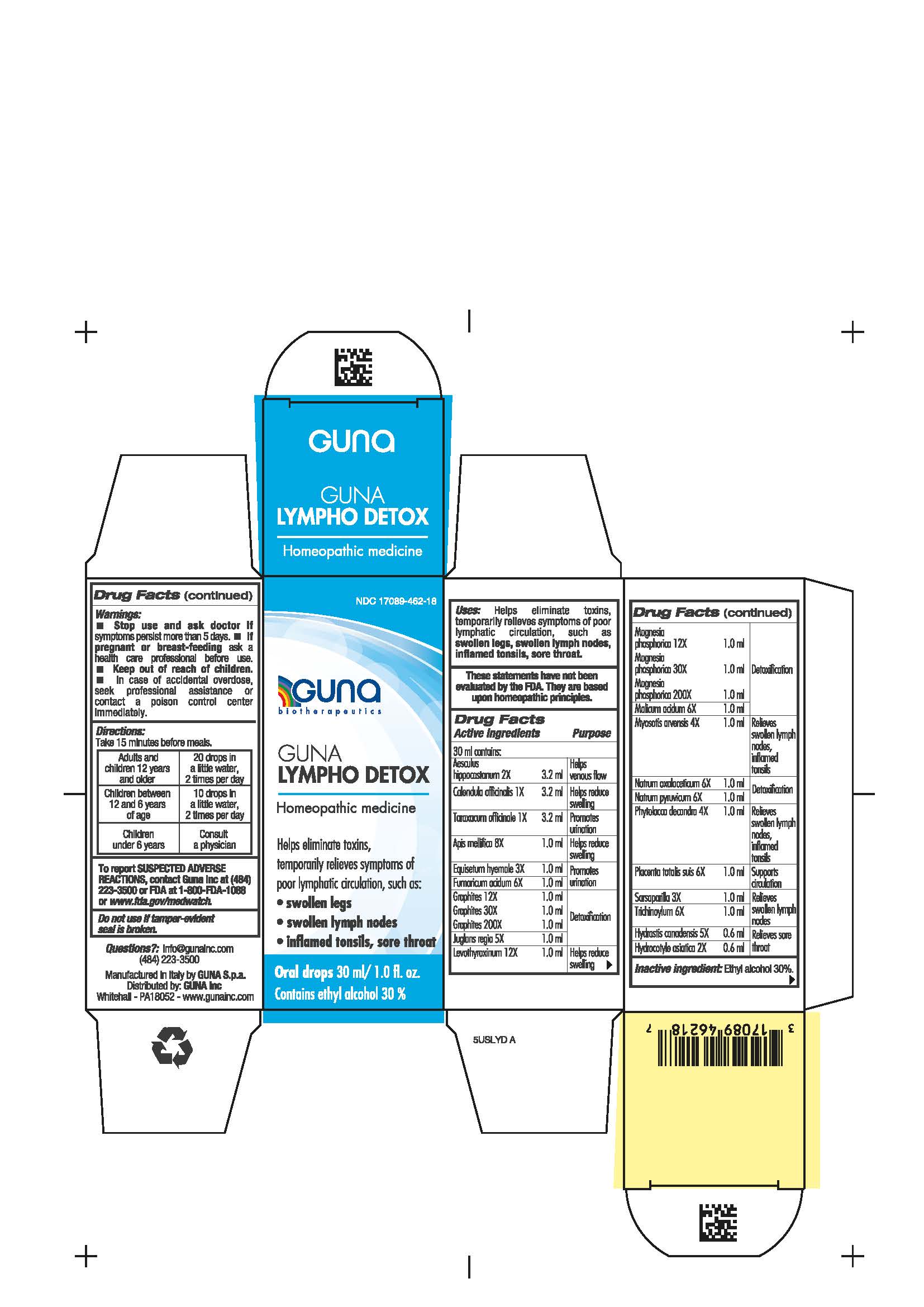 DRUG LABEL: GUNA LYMPHO DETOX
NDC: 17089-462 | Form: SOLUTION/ DROPS
Manufacturer: Guna spa
Category: homeopathic | Type: HUMAN OTC DRUG LABEL
Date: 20201023

ACTIVE INGREDIENTS: APIS MELLIFERA 8 [hp_X]/30 mL; CALENDULA OFFICINALIS FLOWER 1 [hp_X]/30 mL; MALIC ACID 6 [hp_X]/30 mL; EQUISETUM HYEMALE 3 [hp_X]/30 mL; FUMARIC ACID 6 [hp_X]/30 mL; GRAPHITE 12 [hp_X]/30 mL; JUGLANS REGIA FRUIT RIND, IMMATURE 5 [hp_X]/30 mL; LEVOTHYROXINE 12 [hp_X]/30 mL; MAGNESIUM PHOSPHATE, DIBASIC TRIHYDRATE 12 [hp_X]/30 mL; MYOSOTIS ARVENSIS 4 [hp_X]/30 mL; SODIUM DIETHYL OXALACETATE 6 [hp_X]/30 mL; SODIUM PYRUVATE 6 [hp_X]/30 mL; PHYTOLACCA AMERICANA ROOT 4 [hp_X]/30 mL; SARSAPARILLA 3 [hp_X]/30 mL; TARAXACUM OFFICINALE 1 [hp_X]/30 mL; DODECAHYDROXYCYCLOHEXANE DIHYDRATE 6 [hp_X]/30 mL; SUS SCROFA PLACENTA 6 [hp_X]/30 mL; HORSE CHESTNUT 2 [hp_X]/30 mL; GOLDENSEAL 5 [hp_X]/30 mL; CENTELLA ASIATICA WHOLE 2 [hp_X]/30 mL
INACTIVE INGREDIENTS: ALCOHOL 9 mL/30 mL

GUNA LYMPHO DETOX

DIRECTIONS

Adults and children 12 years and older: 20 drops in a little water, 2 times per day
Children between 12 years and 6 years of age: 10 drops in a little water, 2 times per day
Children under 6 years: consult a physician

ACTIVE INGREDIENTS/PURPOSE

AESCULUS HIPPOCASTANUM 2X HELPS VENOUS FLOW

CALENDULA OFFICINALIS 1X HELPS REDUCE SWELLING

TARAXACUM OFFICINALE 1X PROMOTES URINATION

APIS MELLIFICA 8X HELPS REDUCE SWELLING

EQUISETUM HYEMALE 3X PROMOTES URINATION

FUMARICUM ACIDUM 6X PROMOTES URINATION

GRAPHITES 12X 30X 200X DETOXIFICATION

JUGLANS REGIA 5X DETOXIFICATION

LEVOTHYROXINUM 12X HELPS REDUCE SWELLING

MAGNESIA PHOSPHORICA 12X 30X 200X DETOXIFICATION

MALICUM ACIDUM 6X DETOXIFICATION

MYOSOTIS ARVENSIS 4X RELIEVES SWOLLEN LYMPH NODES, INFLAMED TONSILS

NATRUM OXALACETICUM 6X DETOXIFICATION

NATRUM PYRUVICUM 6X DETOXIFICATION

PHYTOLACCA DECANDRA 4X RELIEVES SWOLLEN LYMPH NODES, INFLAMED TONSILS

PLACENTA TOTALIS SUIS 6X SUPPORTS CIRCULATION

SARSAPARILLA 3X RELIEVES SWOLLEN LYMPH NODES

TRICHINOYL PHOSPHATE 6X RELIEVES SWOLLEN LYMPH NODES

HYDRASTIS CANADENSIS 5X RELIEVES SORE THROAT

HYDROCOTYLE ASIATICA 2X RELIEVES SORE THROAT

USES

Helps eliminate toxins, temporarily relieves symptoms of poor lymphatic circulation, such as:

- swollen legs
- swollen lymph nodes
- inflamed tonsils, sore throat

WARNINGS

- Stop use and ask doctor if symptoms persist more than 5 days.
- If pregnant or breast-feeding ask a health care professional before use.
- Keep out of reach of children.
- In case of overdose,seek professional assistance or contact a Poison Control Center immediately.
- Contains ethyl alcohol 30%

PREGNANCY

If pregnant or breast-feeding ask a health care professional before use

WARNINGS

Keep out of reach of children

QUESTIONS

Questions?: info@gunainc.com

(484) 223-3500

INDICATIONS AND USAGE

Take 15 minutes before meals

Inactive ingredient: Ethyl alcohol 30%.